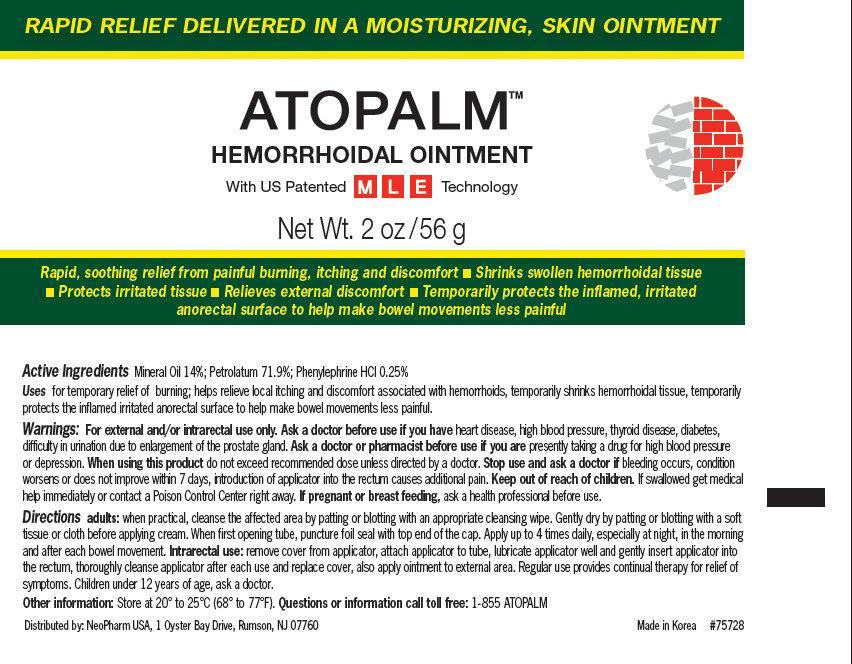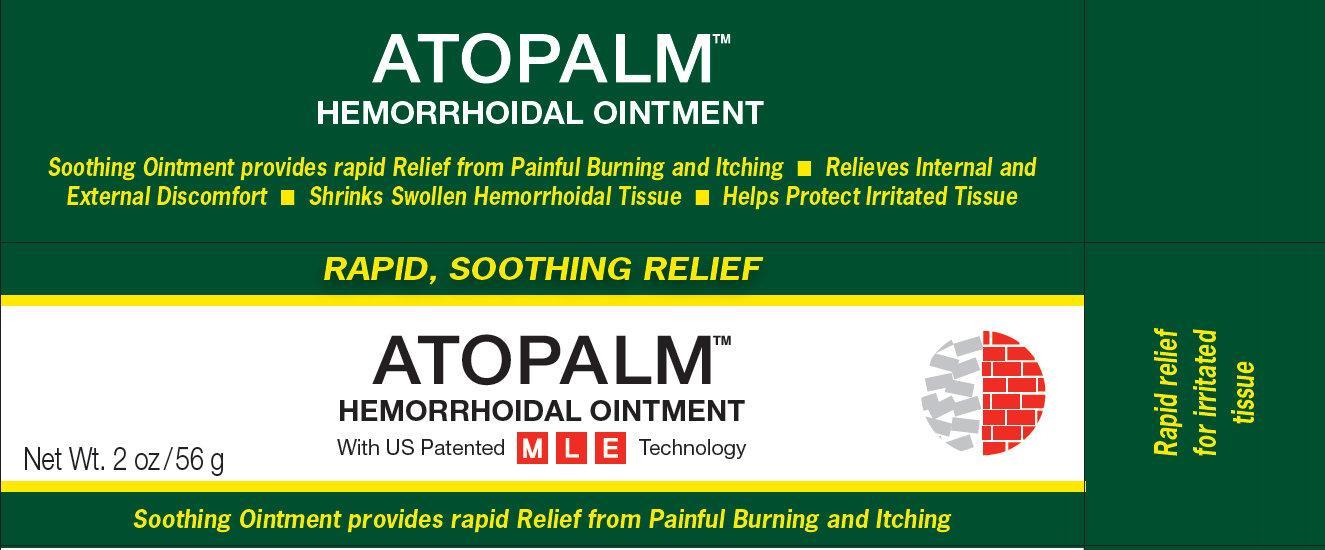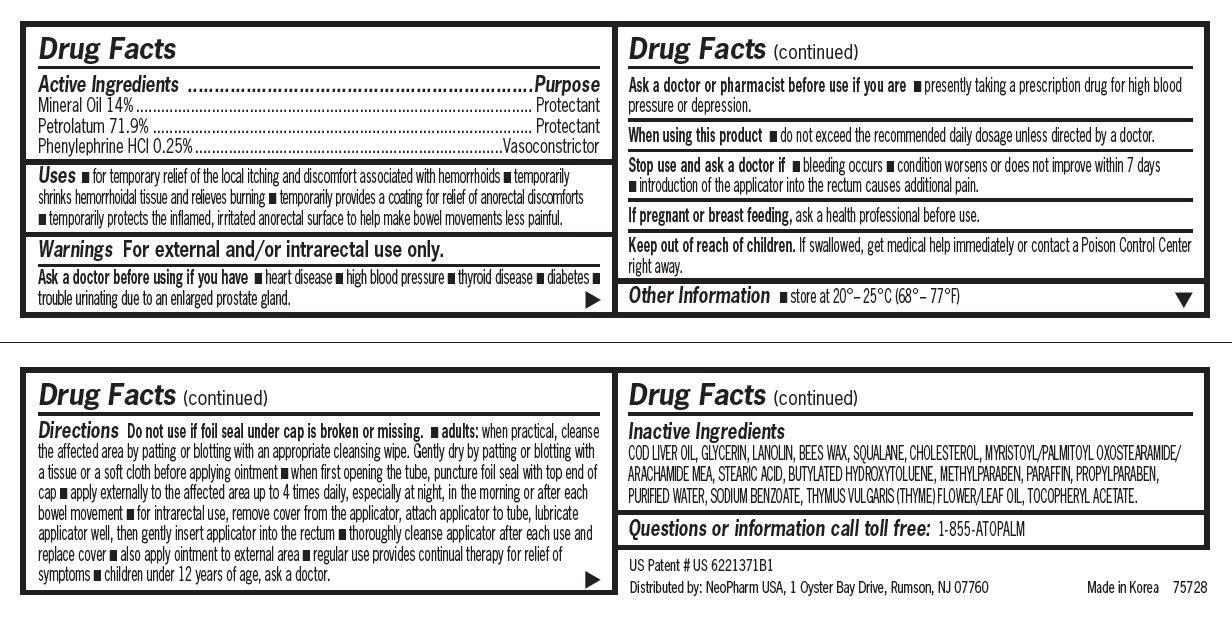 DRUG LABEL: ATOPALM Hemorrhoidal
NDC: 51141-0230 | Form: OINTMENT
Manufacturer: NeoPharm USA
Category: otc | Type: HUMAN OTC DRUG LABEL
Date: 20120718

ACTIVE INGREDIENTS: MINERAL OIL 14 g/100 g; PETROLATUM 71.9 g/100 g; PHENYLEPHRINE HYDROCHLORIDE 0.25 g/100 g
INACTIVE INGREDIENTS: COD LIVER OIL; GLYCERIN; LANOLIN; SQUALANE; CHOLESTEROL; MYRISTOYL/PALMITOYL OXOSTEARAMIDE/ARACHAMIDE MEA; STEARIC ACID; BUTYLATED HYDROXYTOLUENE; METHYLPARABEN; PROPYLPARABEN; PARAFFIN; WATER; SODIUM BENZOATE; THYME OIL; .ALPHA.-TOCOPHEROL ACETATE

ATOPALM Hemorrhoidal Ointment

Active Ingredients

Mineral Oil 14%

Petrolatum 71.9%

Phenylephrine HCl 0.25%

Purpose

Protectant
Protectant
Vascocontrictor

Uses

■ for temporary relief of the local itching and discomfort associated with hemorrhoids

■ temporarily shrinks hemorrhoidal tissue and relieves burning

■ temporarily provides a coating for relief of anorectal discomforts

■ temporarily protects the inflamed, irritated anorectal surface to help make bowel movements less painful.

Warnings

For external and/or intrarectal use only.

Ask a doctor before using if you have

■ heart disease ■ high blood pressure ■ thyroid disease ■ diabetes ■ trouble urinating due to an enlarged prostate gland

Ask a doctor of pharmacist before use if you are

■ presently taking a prescription drug for high blood pressure or depression.

When using this product

■ do not exceed the recommended daily dosage unless directed by a doctor

Stop use and ask a doctor if

■ bleeding occurs
■ condition worsens or does not improve within 7 days
■ introduction of the applicator into the rectum causes additional pain.

If pregnant or breast feeding,

ask a health professional before use.

Keep out of reach of children.

If swallowed, get medical help immediately or contact a Poison Control Center right away.

Directions

Do not use if foil seal under cap is broken or missing.
■ adults: when practical, cleanse the affected area by patting or blotting with an appropriate cleansing wipe. Gently dry by patting or blotting with a tissue or a soft cloth before applying ointment
■ when first opening the tube, puncture foil seal with top end of cap
■ apply externally to the affected area up to 4 times daily, especially at night, in the morning or after each bowel movement
■ for intrarectal use, remove cover from the applicator, attach applicator to tube, lubricate applicator well, then gently insert applicator into the rectum
■ thoroughly cleanse applicator after each use and replace cover
■ also apply ointment to external area
■ regular use provides continual therapy for relief of
symptoms
■ children under 12 years of age, ask a doctor.

STORAGE AND HANDLING

store at 20° – 25°C (68° – 77°F)

Inactive Ingredients

COD LIVER OIL, GLYCERIN, LANOLIN, BEES WAX, SQUALANE, CHOLESTEROL, MYRISTOYL/PALMITOYL OXOSTEARAMIDE/ARACHAMIDE MEA, STEARIC ACID, BUTYLATED HYDROXYTOLUENE, METHYLPARABEN, PARAFFIN, PROPYLPARABEN, PURIFIED WATER, SODIUM BENZOATE, THYMUS VULGARIS (THYME) FLOWER/LEAF OIL, TOCOPHERYL ACETATE.

Questions or information call toll free

1-855- ATOPALM

ATOPALM Hemorrhoidal Ointment 2oz (51141-0230-2)

Outer Package
Inner Package